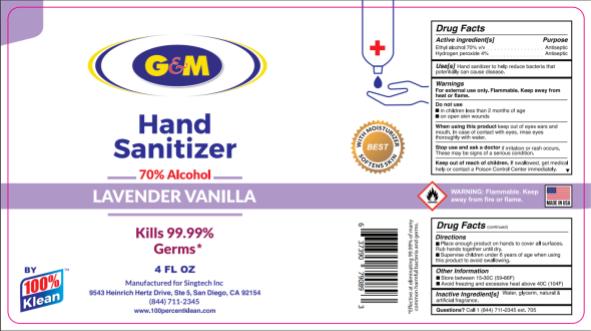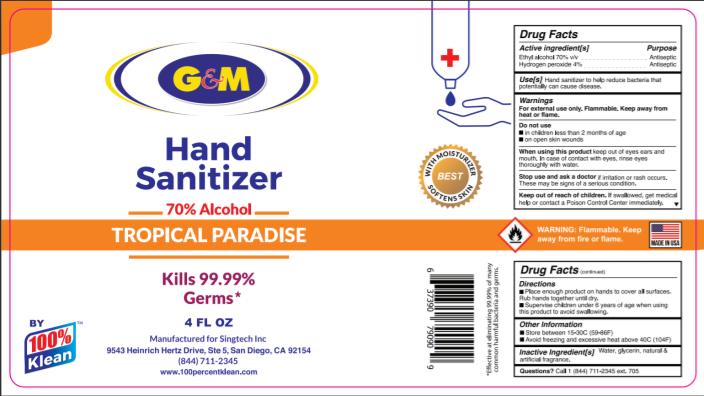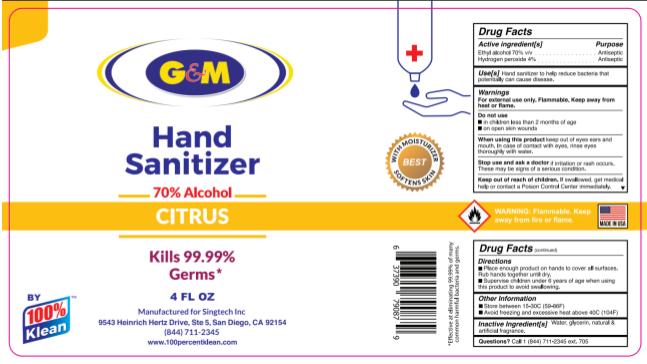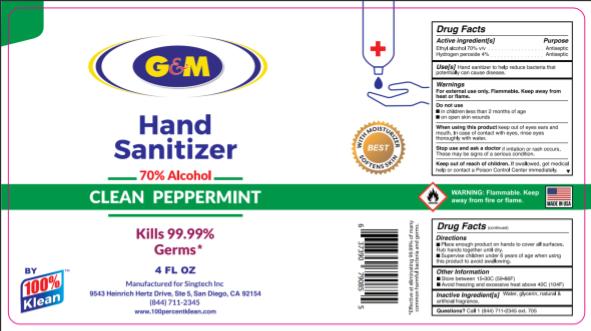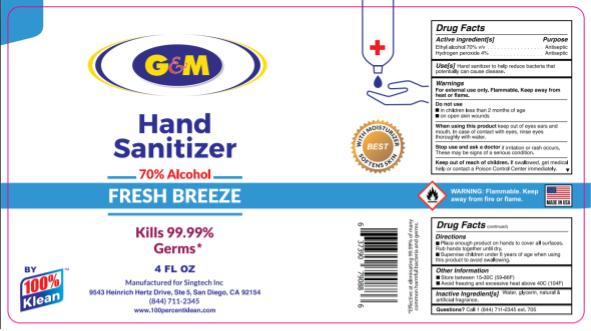 DRUG LABEL: Hand Sanitizer
NDC: 75334-031 | Form: AEROSOL, SPRAY
Manufacturer: Singtech Inc.
Category: otc | Type: HUMAN OTC DRUG LABEL
Date: 20210120

ACTIVE INGREDIENTS: HYDROGEN PEROXIDE 4 mL/100 mL; ALCOHOL 70 mL/100 mL
INACTIVE INGREDIENTS: PEPPERMINT; GLYCERIN 1.45 mL/100 mL; WATER; VACCINIUM MYRTILLUS ANTHOCYANOSIDES

100%Klean Hand Sanitizers Scented

Active Ingredient(s)

Isopropyl Alcohol 70% v/v. Purpose: Antiseptic

Hydrogen Peroxide 4% Purpose: Antiseptic

Purpose

Antiseptic, Hand Sanitizer

Use

Hand Sanitizer to help reduce bacteria that potentially can cause disease.

Warnings

For external use only. Flammable. Keep away from heat or flame

Do not use

- in children less than 2 months of age
- on open skin wounds

When using this product keep out of eyes, ears, and mouth. In case of contact with eyes, rinse eyes thoroughly with water.
Stop use and ask a doctor if irritation or rash occurs. These may be signs of a serious condition.
Keep out of reach of children. If swallowed, get medical help or contact a Poison Control Center right away.

Stop use and ask a doctor if irritation or rash occurs. These may be signs of a serious condition.

Keep out of reach of children. If swallowed, get medical help or contact a Poison Control Center right away.

Directions

- Place enough product on hands to cover all surfaces. Rub hands together until dry.
- Supervise children under 6 years of age when using this product to avoid swallowing.

Other information

- Store between 15-30C (59-86F)
- Avoid freezing and excessive heat above 40C (104F)

Inactive ingredients

water, glycerin, natural and artificial fragrances.

Package Label - Principal Display Panel

75334-034-03

PACKAGE LABEL

75334-031-03

PACKAGE LABEL

75334-032-03

PACKAGE LABEL

75334-033-03

PACKAGE LABEL

75334-025-03